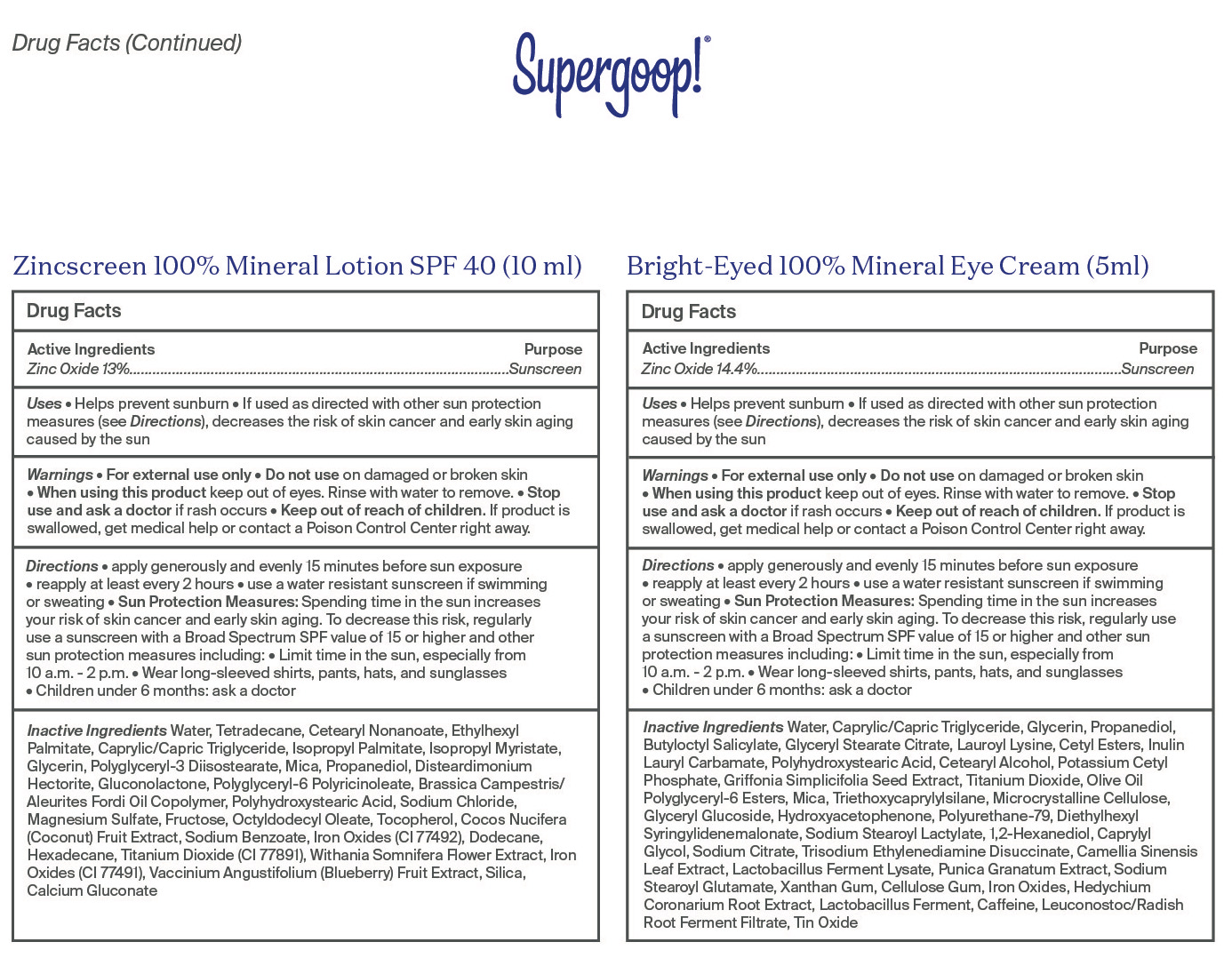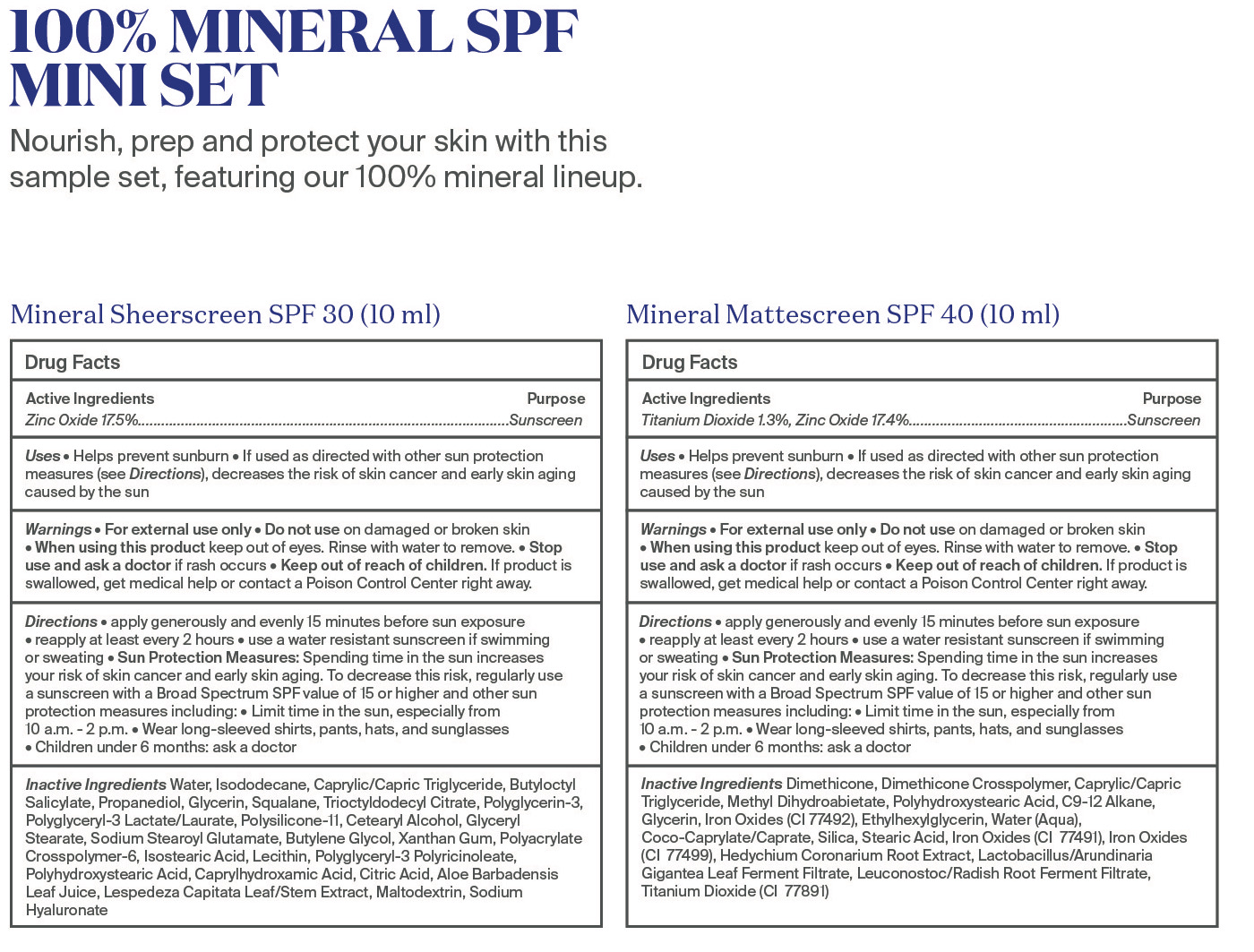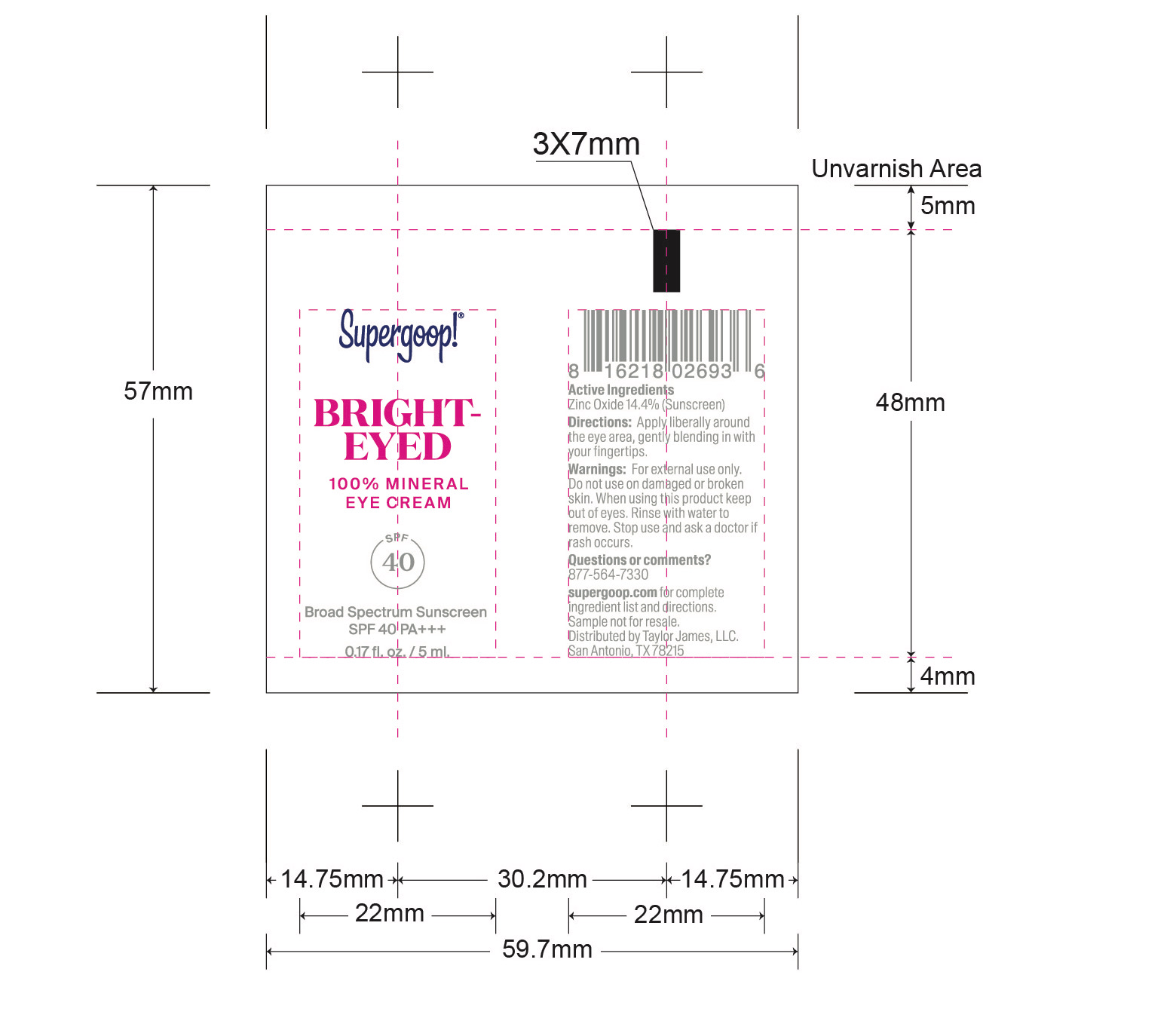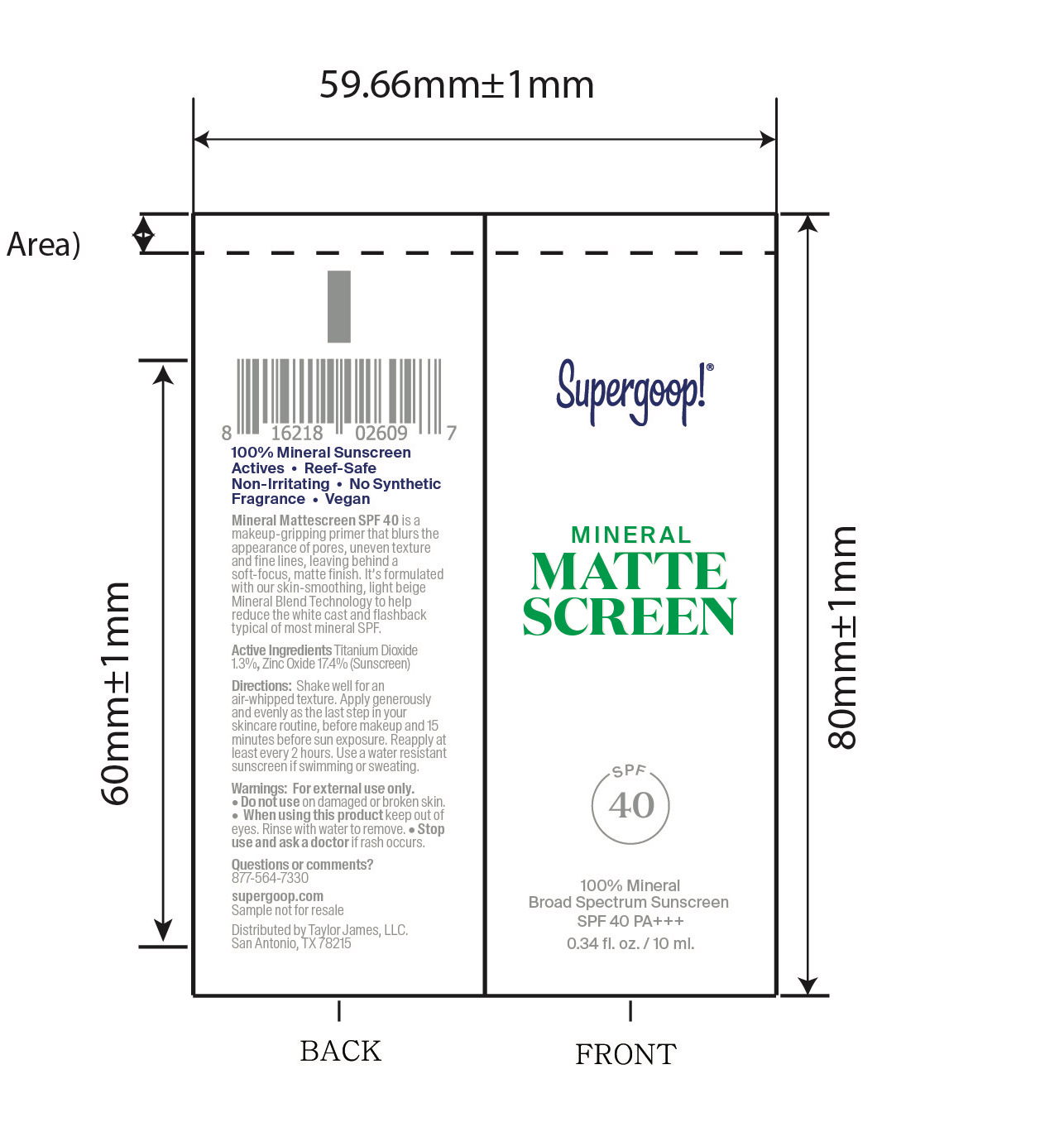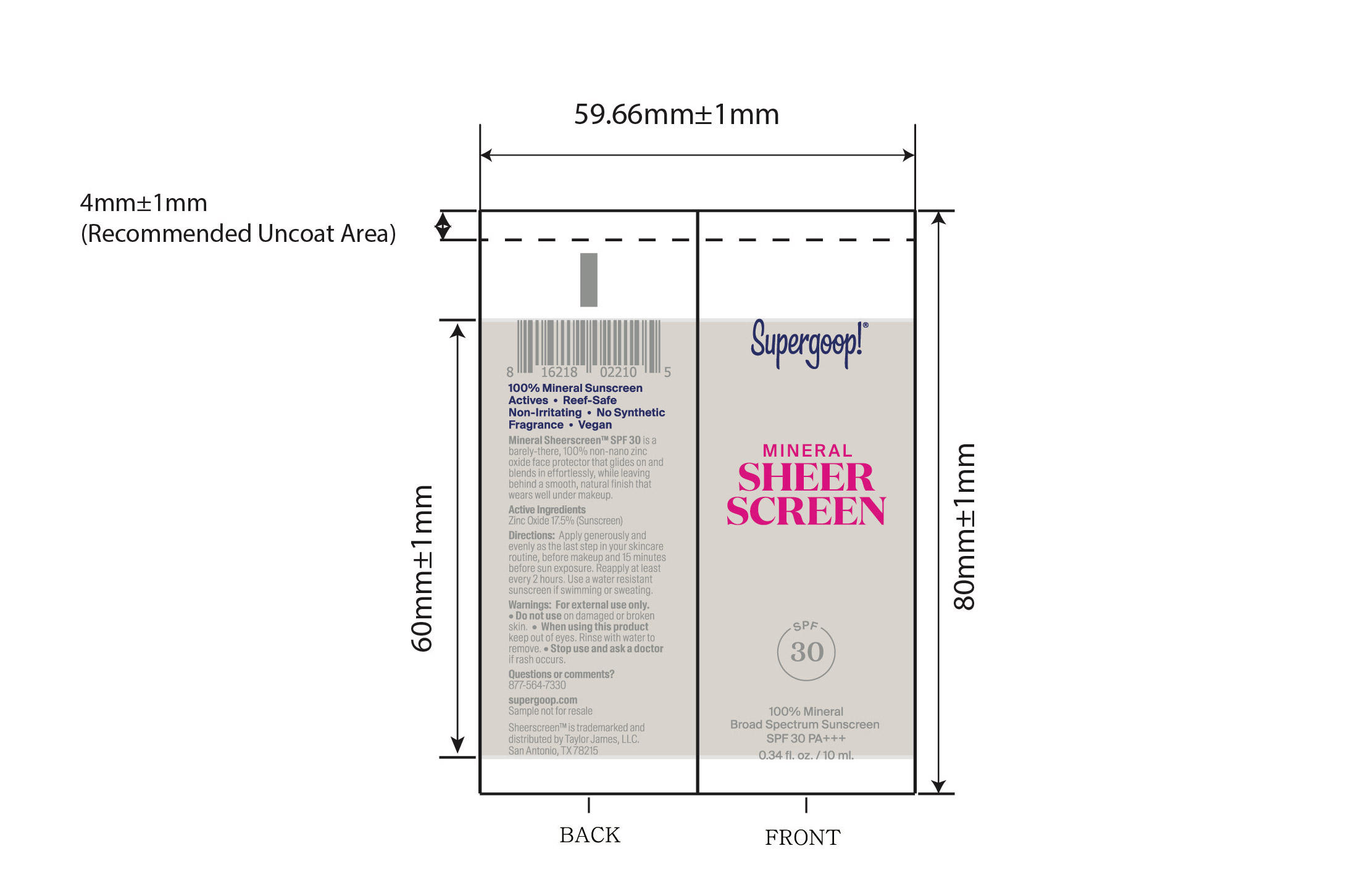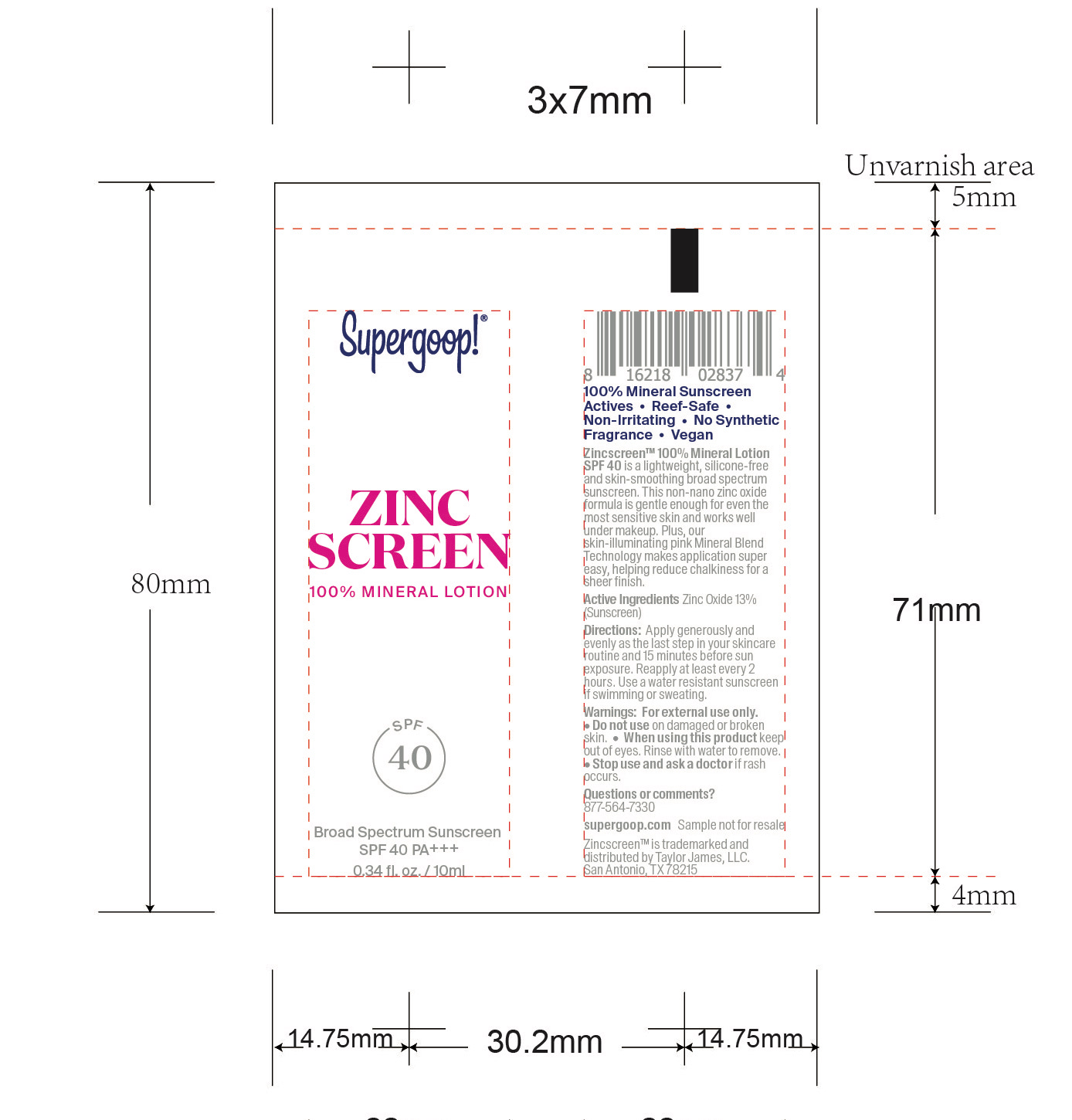 DRUG LABEL: 100 % Mineral SPF Mini Set
NDC: 82384-0020 | Form: KIT | Route: TOPICAL
Manufacturer: System Beauty, LLC
Category: otc | Type: HUMAN OTC DRUG LABEL
Date: 20211209

ACTIVE INGREDIENTS: ZINC OXIDE 17.5 g/100 mL; ZINC OXIDE 17.4 g/100 mL; TITANIUM DIOXIDE 1.3 g/100 mL; ZINC OXIDE 13 g/100 mL; ZINC OXIDE 14.4 g/100 mL
INACTIVE INGREDIENTS: MALTODEXTRIN; GLYCERYL MONOSTEARATE; SODIUM STEAROYL GLUTAMATE; BUTYLENE GLYCOL; AMMONIUM ACRYLOYLDIMETHYLTAURATE, DIMETHYLACRYLAMIDE, LAURYL METHACRYLATE AND LAURETH-4 METHACRYLATE COPOLYMER, TRIMETHYLOLPROPANE TRIACRYLATE CROSSLINKED (45000 MPA.S); POLYHYDROXYSTEARIC ACID (2300 MW); ISODODECANE; MEDIUM-CHAIN TRIGLYCERIDES; ISOSTEARIC ACID; LECITHIN, SOYBEAN; BUTYLOCTYL SALICYLATE; PROPANEDIOL; GLYCERIN; SQUALANE; POLYGLYCERIN-3; CETOSTEARYL ALCOHOL; XANTHAN GUM; POLYGLYCERYL-3 PENTARICINOLEATE; HYALURONATE SODIUM; WATER; DIMETHICONE/VINYL DIMETHICONE CROSSPOLYMER (SOFT PARTICLE); TRIOCTYLDODECYL CITRATE; CAPRYLHYDROXAMIC ACID; CITRIC ACID MONOHYDRATE; ALOE VERA LEAF; FERRIC OXIDE YELLOW; FERROSOFERRIC OXIDE; LEUCONOSTOC/RADISH ROOT FERMENT FILTRATE; HEDYCHIUM CORONARIUM ROOT; MEDIUM-CHAIN TRIGLYCERIDES; GLYCERIN; DIMETHICONE; DIMETHICONE CROSSPOLYMER (450000 MPA.S AT 12% IN CYCLOPENTASILOXANE); POLYHYDROXYSTEARIC ACID (2300 MW); ETHYLHEXYLGLYCERIN; SILICON DIOXIDE; METHYL DIHYDROABIETATE; WATER; COCO-CAPRYLATE/CAPRATE; STEARIC ACID; FERRIC OXIDE RED; ETHYLHEXYL PALMITATE; SILICON DIOXIDE; WATER; CETEARYL NONANOATE; SODIUM CHLORIDE; MAGNESIUM SULFATE ANHYDROUS; FRUCTOSE; FERRIC OXIDE YELLOW; HEXADECANE; ISOPROPYL PALMITATE; OCTYLDODECYL OLEATE; CALCIUM GLUCONATE; SODIUM BENZOATE; TETRADECANE; GLUCONOLACTONE; LOWBUSH BLUEBERRY; POLYGLYCERYL-6 POLYRICINOLEATE; POLYHYDROXYSTEARIC ACID (2300 MW); TOCOPHEROL; COCONUT; POLYGLYCERYL-3 DIISOSTEARATE; GLYCERIN; WITHANIA SOMNIFERA FLOWER; FERRIC OXIDE RED; MEDIUM-CHAIN TRIGLYCERIDES; DODECANE; TITANIUM DIOXIDE; ISOPROPYL MYRISTATE; MICA; PROPANEDIOL; DISTEARDIMONIUM HECTORITE; GRIFFONIA SIMPLICIFOLIA SEED; MICA; HYDROXYACETOPHENONE; CARBOXYMETHYLCELLULOSE SODIUM, UNSPECIFIED FORM; FERRIC OXIDE RED; POLYHYDROXYSTEARIC ACID (2300 MW); SODIUM CITRATE; GREEN TEA LEAF; PUNICA GRANATUM ROOT BARK; SODIUM STEAROYL GLUTAMATE; PROPANEDIOL; 1,2-HEXANEDIOL; CAPRYLYL GLYCOL; TITANIUM DIOXIDE; SODIUM STEAROYL LACTYLATE; CAFFEINE; WATER; GLYCERIN; CETYL ESTERS WAX; TRISODIUM ETHYLENEDIAMINE DISUCCINATE; HEDYCHIUM CORONARIUM ROOT; LEUCONOSTOC/RADISH ROOT FERMENT FILTRATE; STANNIC OXIDE; GLYCERYL STEARATE CITRATE; LAUROYL LYSINE; CETOSTEARYL ALCOHOL; XANTHAN GUM; MEDIUM-CHAIN TRIGLYCERIDES; BUTYLOCTYL SALICYLATE; POTASSIUM CETYL PHOSPHATE; OLIVE OIL POLYGLYCERYL-6 ESTERS; TRIETHOXYCAPRYLYLSILANE; MICROCRYSTALLINE CELLULOSE; DIETHYLHEXYL SYRINGYLIDENEMALONATE

100% Mineral SPF Mini Set

Zincscreen 100% Mineral Lotion SPF 40 Active

Active Ingredients Purpose

Zinc Oxide 13% Sunscreen

Mineral Mattescreen SPF 40 active

Active Ingredients Purpose

Titanium Dioxide 1.3% Sunscreen

Zinc Oxide 17.4% Sunscreen

Bright-Eyed 100% Mineral Eye Cream active

Active Ingredients Purpose

Zinc Oxide 14.4% Sunscreen

Mineral Sheerscreen SPF 30 active

Active Ingredients Purpose

Zinc Oxide 17.5% Sunscreen

Uses

- Helps prevent sunburn
- If used as directed with other sun protection measures (see Directions), decreases the risk of skin cancer and early skin aging caused by the sun

Keep out of reach of children. If product is swallowed, get medical help or contact a Poison Control Center right away.

Stop use and ask a doctor if rash occurs

Warnings

For external use only

Do not use on damaged or broken skin

When using this product keep out of eyes

Directions

- apply generously and evenly 15 minutes before sun exposure
- reapply at least every 2 hours
- use a water resistant sunscreen if swimming or sweating
- Sun Protection Measures: Spending time in the sun increases your risk of skin cancer and early skin aging. To decrease this risk, regularly use a sunscreen with a Broad Spectrum SPF value of 15 or higher and other sun protection measures including:
- Limit time in the sun, especially from 10 a.m. - 2 p.m.
- Wear long-sleeved shirts, pants, hats, and sunglassess
- Children under 6 months: Ask a doctor.

Zincscreen 100% Mineral Lotion SPF 40 Inactive ingredients

Inactive Ingredients

Water, Tetradecane, Cetearyl Nonanoate, Ethylhexyl Palmitate, Caprylic/Capric Triglyceride, Isopropyl Myristate, Glycerin, Polyglyceryl-3 Diisostearate, Mica, Propanediol, Disteardimonium Hectorite, Gluconolactone, Polyglyceryl-6 Polyricinoleate, Brassica Campestris/Aleurites Fordi Oil Copolymer, Polyhydrostearic Acid, Sodium Chloride, Magnesium Sulfate, Fructose, Octyldodecyl Oleate, Tocopherol, Cocos Nucifera (Coconut) Fruit Extract, Sodium Benzoate, Iron oxides (CI 77492), Dodecane, Hexadecane, Titanium Dioxide (CI 77891), Withania Somnifera Flower Extract, Iron Oxides (CI 77491), Vaccinium Angustifolia (Blueberry) Fruit Extract, Silica, Calcium Gluconate

Mineral Mattescreen SPF 40 Inactive Ingredients

Inactive Ingredients

Dimethicone, Dimethicone Copolymer, Caprylic/Capric Triglyceride, Methyl Dihydroabietate, Polyhydroxystearic Acid, C9-12 Alkane, Glycerin, Iron Oxides (CI 77492), Ethylhexylglycerin, Water (Aqua), Coco-Caprylate/Caprate, Silica, Stearic Acid, Iron Oxides (CI 77491), Iron Oxides (CI 77499), Hedychium Coronarium Root Extract, Lactobacillus/Arundinaria Gigantea Leaf Ferment Filtrate, Leuconostoc/Radish Root Ferment Filtrate, Titanium Dioxide (CI 77891)

Bright-Eyed Mineral Eye Cream SPF 40 inactive ingredients

Inactive Ingredients Water, Caprylic/Capric Triglyceride, Glycerin, Propanediol, Butyloctyl Salicylate, Glyceryl Stearate Citrate, Lauroyl Lysine, Cetyl Esters, Inulin Lauryl CarbamatePolyhydroxystearic Acid, Cetearyl Alcohol, Potassium Cetyl phosophate, Griffonia Simplicifolia Seed Extract, Titanium Dioxide, Olive Oil Polyglyceryl-6 Esters, Mica, Triethoxycaprylylsilane, Microcrystalline cellulose, Glyceryl Glucoside, Hydroxyacetophenone, Polyurethane-79, Diethylhexyl Syringylidenemalonate, Sodium Stearoyl Lactylate, 1,2-Hexanediol, Caprylyl Glycol, Sodium Citrate, Trisodium Ethylenediamine Disuccinate, Camellia Sinensis Leaf Extract, Lactobacillus Ferment Lysate, Punica Granatum Extract, Sodium Citrate, Sodium Stearoyl Glutamate, Xanthan Gum, Cellulose Gum, Iron Oxides, Hedychium Coronarium Root Extract, Lactobacillus Ferment, Caffeine, Leuconostoc/Radish Root Ferment Filtrate, Tin Oxide.

Mineral Sheerscreen SPF 30 Inactive ingredients

Inactive ingredients

Water, Isododecane, Caprylic/Capric Triglyceride, Butyloctyl Salicylate, Propanedlol, Glycerin, Squalane, Trioctyldodecyl Citrate, Polyglycerin-3, Polyglyceryl-3 Lactate/Laurate, Polysilicone-11, Cetearyl Alcohol, Glyceryl Stearate, Sodium Stearoyl Glutamate, Butylene Glycol, Xanthan Gum, Polyacrylate Crosspolymer-6, lsostearic Acid, Lecithin, Polyglyceryl-3 Polyricinoleate, Polyhydroxystearic Acid, Caprylhydroxamic Acid, Citric Acid, Aloe Barbadensis Leaf Juice, Lespedeza Capitata Leaf/Stem Extract, Maltodextrin, Sodium Hyaluronate

100% Mineral SPF Mini Set

Nourish, prep and protect your skin with this sample set, featuring our 100% mineral lineup

Mineral Sheerscreen SPF 30 (10 ml)

Mineral Mattescreen SPF 40 (10 ml)

Zincscreen 100% Mineral Lotion SPF 40 (10 ml)

Bright-eyed 100% Mineral Eye Cream (5 ml)

Zincscreen 100% Mineral SPF 40

Zincscreen 100% Mineral Lotion

SPF 40

Broad Spectrum SunscreenSPF 40 PA+++

0.34 fl oz./ 10ml

Mineral Mattescreen SPF 40

Mineral Mattescreen

SPF 40

100% Mineral

Broad Spectrum Sunscreen

SPF 40 PA+++

0.34 fl. oz. /10 ml

Bright-eyed Mineral Eye Cream SPF 40

Bright-eyed

100% Mineral Eye Cream

SPF 40

Broad Spectrum Sunscreen SPF 40 PA +++

0.17 fl.oz. / 5 ml

Mineral Sheerscreen SPF 30

Mineral Sheerscreen

SPF 30

100% Mineral Broad Spectrum Sunscreen SPF 30 PA+++

0.34 fl. oz.